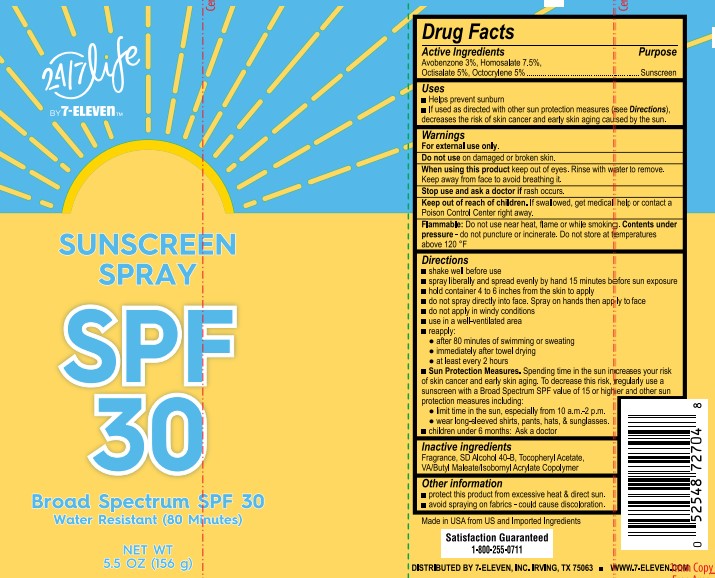 DRUG LABEL: 7-Eleven
NDC: 13630-0239 | Form: SPRAY
Manufacturer: Prime Packaging, Inc.
Category: otc | Type: HUMAN OTC DRUG LABEL
Date: 20220805

ACTIVE INGREDIENTS: HOMOSALATE 62.1 g/1 mL; OCTOCRYLENE 41.4 g/1 mL; OCTISALATE 41.4 g/1 mL; AVOBENZONE 24.8 g/1 mL
INACTIVE INGREDIENTS: ALCOHOL; ALPHA-TOCOPHEROL ACETATE

24/7 Life 7-Eleven Sunscreen Spray SPF 30

Purpose

Sunscreen

Active Ingredients

Avobenzone 3%

Homosalate 7.5%

Octisalate 5%

Octocrylene 5%

Uses

Helps prevent sunburn

If used as directed with other sun protection measures (see Directions), decreases the risk of skin cancer and early skin aging caused by the sun.

Warnings

For external use only.

Do not use

on damaged or broken skin.

When using this product

keep out of eyes. Rinse with water to remove. Keep away from face to avoid breathing it.

Keep out of reach of children.

If product is swallowed, get medical help or contact a Poison Control Center right away.

Flammable

Do not use near heat, flame or while smoking.

Contents under pressure - do not puncture or incinerate.

Do not store at temperatures above 120ºF.

Directions

- shake well before use
- Spray liberally 15 minutes before sun exposure
- hold container 4 to 6 inches from the skin to apply
- do not spray directly into face. Spray on hands then apply to face.
- do not apply in windy conditions
- use in a well-ventilated area
- reapply:
- after 80 minutes of swimming or sweating
- immediately after towel drying
- at least every 2 hours
- Sun Protection Measures. Spending time in the sun increases your risk of skin cancer and early skin aging. To decrease this risk, regularly use a sunscreen with a broad spectrum SPF of 15 or higher and other sun protection measures including:
- limit time in the sun, especially from 10 a.m. - 2 p.m.
- wear long-sleeve shirts, pants, hats, and sunglasses
- children under 6 months: Ask a doctor

Inactive Ingredients

Fragrance, SD Alcohol 40-B, Tocopheryl Acetate, VA/Butyl Maleate/Isobromyl Acrylate Copolymer

Other Information

- Protect this product from excessive heat and direct sun.
- Avoid spraying on fabrics - could cause discoloration.